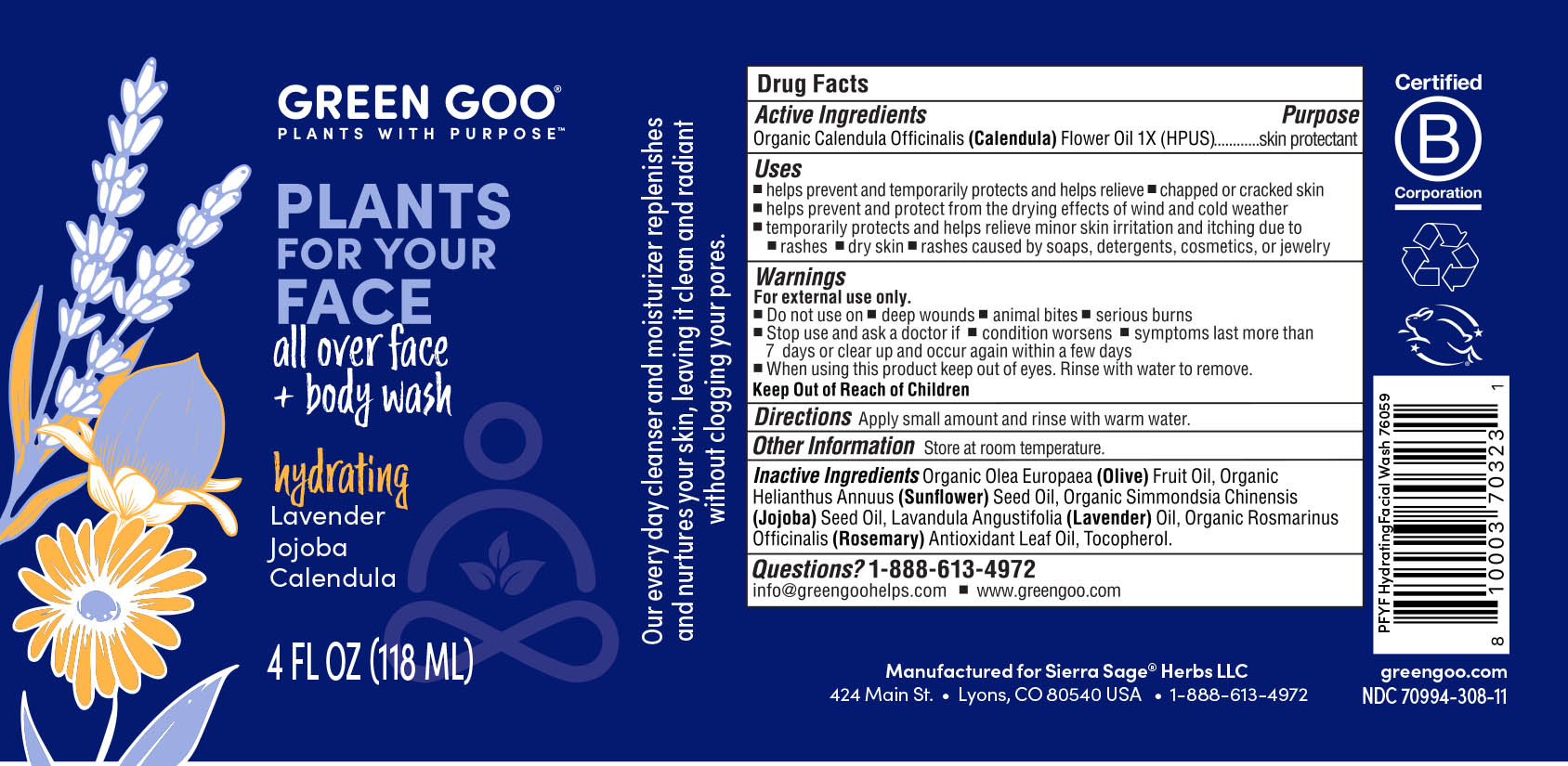 DRUG LABEL: Hydrating Face Wash
NDC: 70994-306 | Form: OIL
Manufacturer: Spry Life LLC
Category: homeopathic | Type: HUMAN OTC DRUG LABEL
Date: 20251215

ACTIVE INGREDIENTS: CALENDULA OFFICINALIS FLOWER 1 [hp_X]/133 mL
INACTIVE INGREDIENTS: LAVENDER OIL; JOJOBA OIL; ROSEMARY OIL; OLIVE OIL; SUNFLOWER OIL; ALPHA-TOCOPHEROL

Hydrating Face Wash

Purpose Section

Skin Protectant

Active Ingredients

Organic Calendula Officinalis (Calendula) Flower Oil 1X (HPUS)

Indications & Usage

■ helps prevent and temporarily protects and helps relieve ■ chapped or cracked skin

■ helps prevent and protect from the drying effects of wind and cold weather

■ temporarily protects and helps relieve minor skin irritation and itching due to

■ rashes ■ dry skin ■ rashes caused by soaps, detergents, cosmetics, or jewelry

Keep out of reach of children section

Keep out of reach of children.

Warnings Section

Warnings

For external use only.

■ Do not use on ■ on deep wounds ■ animal bites ■ serious burns
■ Stop use and ask a doctor if ■ condition worsens ■ symptoms last more than

7 days or clear up and occur again within a few days
■ When using this product keep out of eyes. Rinse with water to remove.

Storage

Store at room temperature.

Dosage & Administration Section

Apply small amount and rinse with warm water.

Inactive Ingredients

Organic Olea Europae (Olive) Fruit Oil, Organic Hlianthus Annuus (Sunflower) Seed Oil, Organic Simmondsia Chinesis (Jojoba) Seed Oil, Tocopherol (Vitamin E), Lavandula Angustifolia (Lavender) Oil, Rosmarinus Officinalis (Rosemary) Leaf Oil.